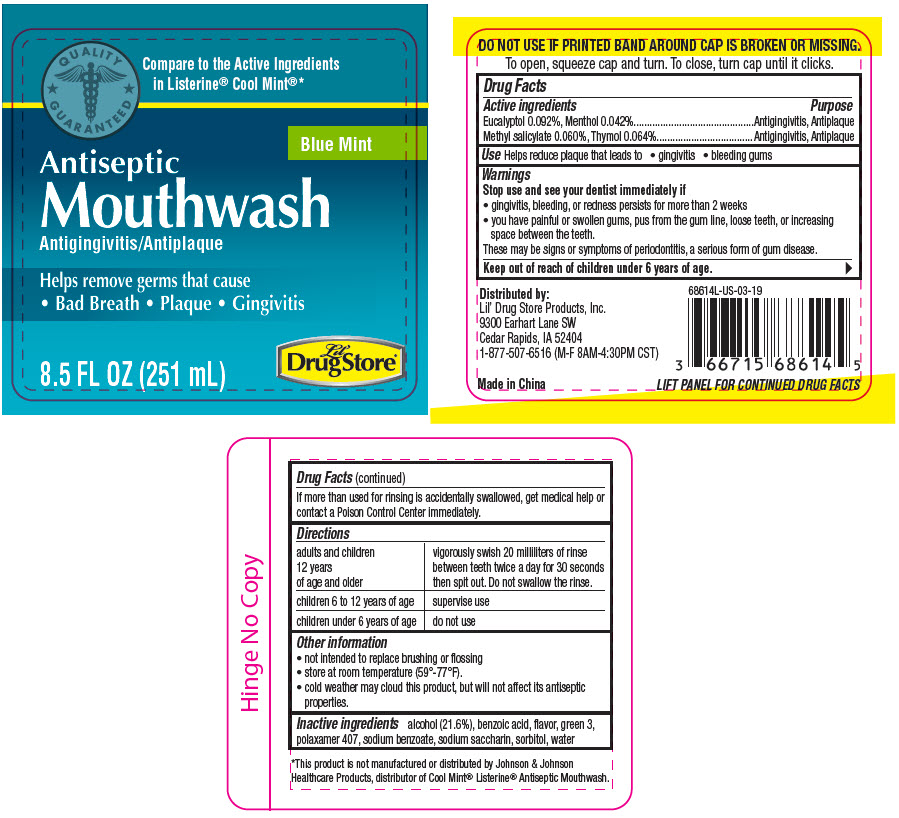 DRUG LABEL: Antiseptic
NDC: 66715-6861 | Form: LIQUID
Manufacturer: Lil' Drug Store Products, Inc
Category: otc | Type: HUMAN OTC DRUG LABEL
Date: 20241231

ACTIVE INGREDIENTS: EUCALYPTOL 0.92 mg/1 mL; MENTHOL, UNSPECIFIED FORM 0.42 mg/1 mL; METHYL SALICYLATE 0.6 mg/1 mL; THYMOL 0.64 mg/1 mL
INACTIVE INGREDIENTS: WATER; ALCOHOL; SORBITOL; POLOXAMER 407; BENZOIC ACID; SACCHARIN SODIUM; SODIUM BENZOATE; FD&C GREEN NO. 3

Mouthwash
Lil' Drug Store® Products

Drug Facts

ACTIVE INGREDIENT

Active ingredients | Purpose
Eucalyptol 0.092%, Menthol 0.042% | Antigingivitis, Antiplaque
Methyl salicylate 0.060%, Thymol 0.064% | Antigingivitis, Antiplaque

Use

Helps reduce plaque that leads to

- gingivitis
- bleeding gums

Warnings

Stop use and see your dentist immediately if

- gingivitis, bleeding, or redness persists for more than 2 weeks
- you have painful or swollen gums, pus from the gum line, loose teeth, or increasing space between the teeth.

These may be signs or symptoms of periodontitis, a serious form of gum disease.

Keep out of reach of children under 6 years of age.

If more than used for rinsing is accidentally swallowed, get medical help or contact a Poison Control Center immediately.

Directions

adults and children 12 years of age and older | vigorously swish 20 milliliters of rinse between teeth twice a day for 30 seconds then spit out. Do not swallow the rinse.
children 6 to 12 years of age | supervise use
children under 6 years of age | do not use

Other information

- not intended to replace brushing or flossing
- store at room temperature (59°-77°F).
- cold weather may cloud this product, but will not affect its antiseptic properties.

Inactive ingredients

alcohol (21.6%), benzoic acid, flavor, green 3, polaxamer 407, sodium benzoate, sodium saccharin, sorbitol, water

Distributed by:
Lil' Drug Store Products, Inc.
9300 Earhart Lane SW
Cedar Rapids, IA 52404

PRINCIPAL DISPLAY PANEL - 251 mL Bottle Label

QUALITY
⋆ GUARANTEED ⋆

Compare to the Active Ingredients
in Listerine® Cool Mint®*

Blue Mint

Antiseptic
Mouthwash
Antigingivitis/Antiplaque

Helps remove germs that cause
• Bad Breath • Plaque • Gingivitis

8.5 FL OZ (251 mL)

Lil'
Drug Store®